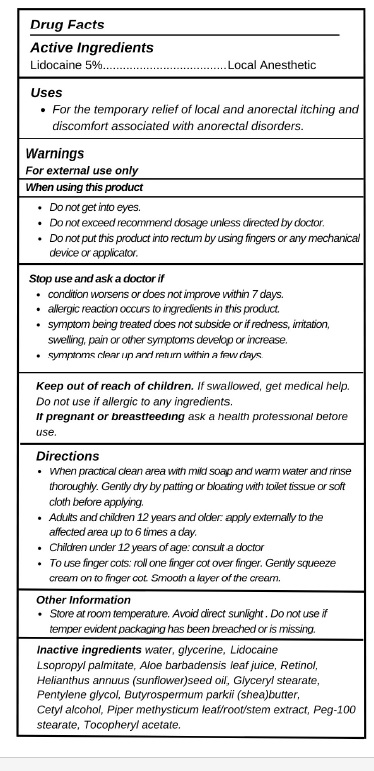 DRUG LABEL: BEAUELI
NDC: 83462-001 | Form: CREAM
Manufacturer: EUbizrival LLC
Category: otc | Type: HUMAN OTC DRUG LABEL
Date: 20230818

ACTIVE INGREDIENTS: LIDOCAINE 5 g/100 g
INACTIVE INGREDIENTS: WATER; GLYCERIN; ALOE; SHEA BUTTER; RETINOL; SUNFLOWER OIL; GLYCERYL STEARATE SE; PENTYLENE GLYCOL; CETYL ALCOHOL; PIPER METHYSTICUM WHOLE; PEG-100 STEARATE; .ALPHA.-TOCOPHEROL ACETATE, D-

Active ingredients

Lidocaine 5%

Purpose

Local Anesthetic

Uses

For the temporary relief of local and anorectal itching and discomfort associated with anorectal disorders.

Warnings

For external use only

When using this product

- Do not get into eyes.
- Do not exceed recommend dosage unless directed by doctor.
- Do not put this product into rectum by using fingers or any mechanical device or applicator.

Stop use and ask a doctor if

- condition worsens or does not improve within 7 days.
- allergic reaction occurs to ingredients in this product.
- symptom being treated does not subside or if redness, irritation, swelling, pain or other symptoms develop or increase.
- symptoms clear up and return within a few days.

Keep out of reach of children.If swallowed, get medical help. Do not use if allergic to any ingredients.

If pregnant or breastfeedingask a health professional before use.

Directions

- When practical clean area with mild soap and warm water and rinse thoroughly. Gently dry by patting or bloating with toilet tissue or soft cloth before applying.
- Adults and children 12 years and older: apply externally to the affected area up to 6 times a day.
- Children under 12 years of age: consult a doctor
- To use finger cots: roll one finger cot over finger. Gently squeeze cream on to finger cot. Smooth a layer of the cream.

Other information

Store at room temperature. Avoid direct sunlight. Do not use if temper evident packaging has been breached or is missing.

INACTIVE INGREDIENT

water, glycerine, Lidocaine Lsopropyl palmitate, Aloe barbadensis leaf juice, Retinol,Helianthus annuus (sunflower)seed oil, Glyceryl stearate,
Pentylene glycol, Butyrospermum parkii (shea)butter,Cetyl alcohol, Piper methysticum leaf/root/stem extract, Peg-100 stearate, Tocopheryl acetate.